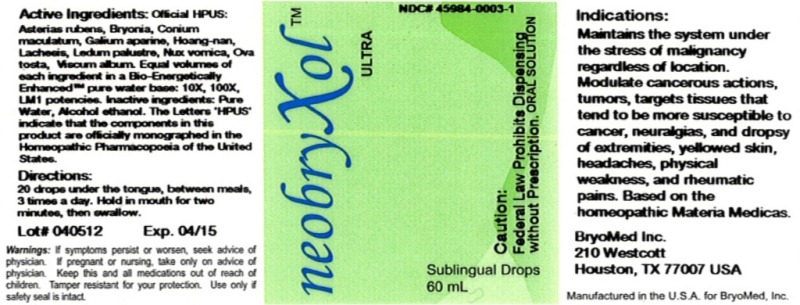 DRUG LABEL: Neobryxol Ultra
NDC: 45984-0003 | Form: LIQUID
Manufacturer: Bryomed Inc.
Category: homeopathic | Type: HUMAN PRESCRIPTION DRUG LABEL
Date: 20120405

ACTIVE INGREDIENTS: ASTERIAS RUBENS 10 [hp_X]/60 mL; BRYONIA ALBA ROOT 10 [hp_X]/60 mL; CONIUM MACULATUM FLOWERING TOP 10 [hp_X]/60 mL; GALIUM APARINE 10 [hp_X]/60 mL; STRYCHNOS WALLICHIANA BARK 10 [hp_X]/60 mL; LACHESIS MUTA VENOM 10 [hp_X]/60 mL; LEDUM PALUSTRE TWIG 10 [hp_X]/60 mL; STRYCHNOS NUX-VOMICA SEED 10 [hp_X]/60 mL; EGG SHELL, COOKED 10 [hp_X]/60 mL; VISCUM ALBUM WHOLE 10 [hp_X]/60 mL
INACTIVE INGREDIENTS: WATER; ALCOHOL

Neobryxol Ultra

Active Ingredients

Official HPUS: Asterias rubens, Bryonia, Conium maculatum Galium aparine, Hoang-nan, Lachesis mutus, Ledum palustre, Nux vomica, Ova tosta and Viscum album.

Reference image ultra.jpg

Inactive Ingredients

Equal volumes of each ingredient in a Bio-Energetically enhanced pure water base: 10X, 100X, LM1 potency. Inactive ingredients: pure water and Alcohol.

Reference image ultra.jpg

Dosage and Administration

Directions: 20 drops under the tongue, between meals, 3 times a day. Hold in mouth for two minutes, then swallow.

Reference image ultra.jpg

Indications and Usage

Maintains the system under the stress of malignancy regardless of location. Modulate cancerous action, tumors, targets tissues that tend to be more susceptible to cancer, neuralgias, and dropsy of extremities, and rheumatic pains. Based on the homeopathic Materia Medicas.

Reference image ultra.jpg

Warnings

If symptoms persist or worsen, seek advice of physician. If pregnant or nursing take only on advice of physician. Keep this and all medication out of reach of children.

Tamper resistant for your protection. Use only if safety seal is intact.

Reference image ultra.jpg

KEEP OUT OF REACH OF CHILDREN

Keep this and all medication out of reach of children.

Reference image ultra.jpg

Purpose

Maintains the system under the stress of malignancy regardless of location.

- Modulate cancerous action
- tumors
- targets tissues that tend to be more susceptible to cancer
- neuralgias and dropsy of extremities
- rheumatic pains

Based on the homeopathic Materia Medicas.
Reference image ultra.jpg

PACKAGE LABEL

BryoMed Inc.

210 Westcott

Houston, TX 77007

Questions call 714-785-4473

Reference image ultra.jpg